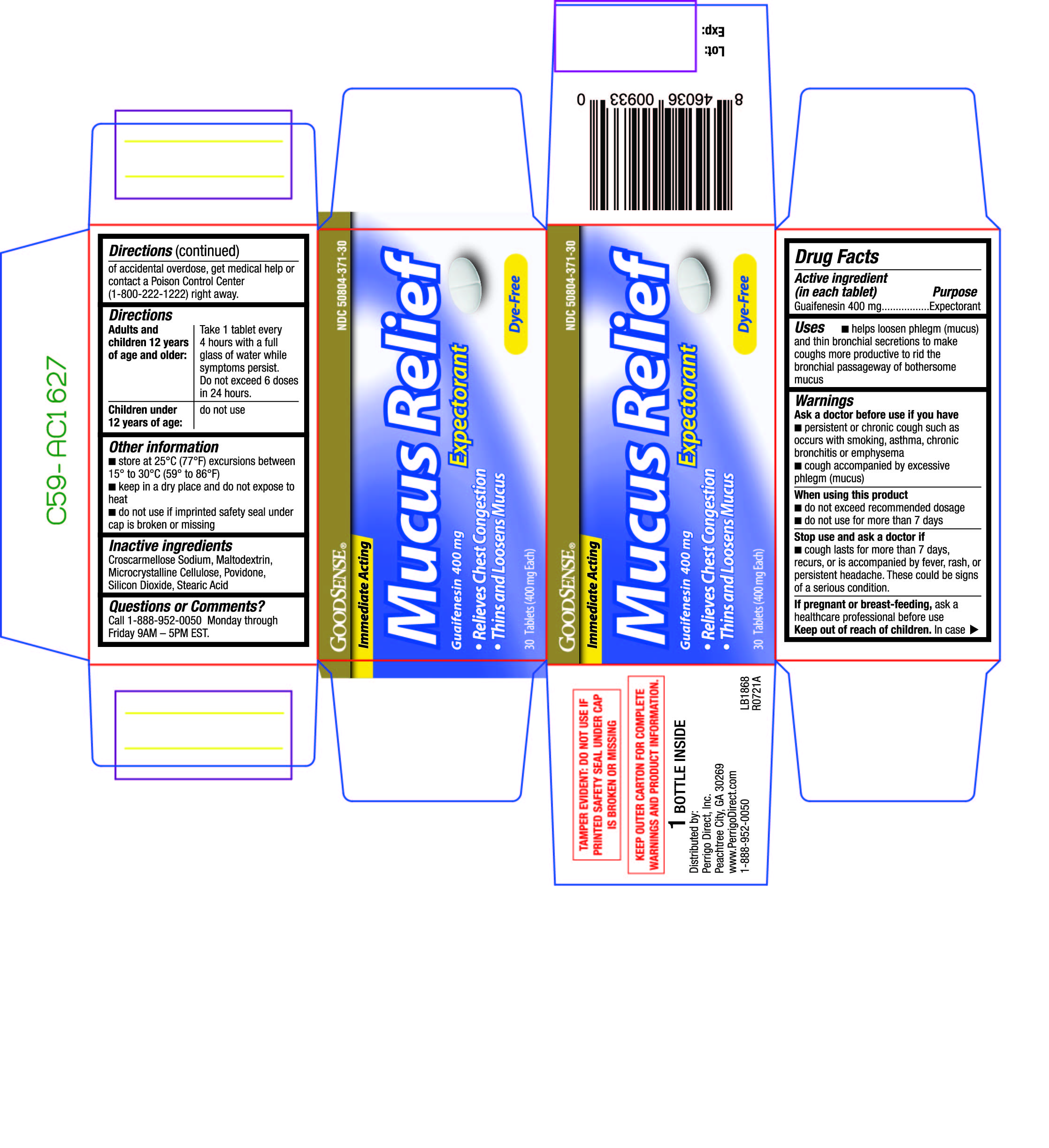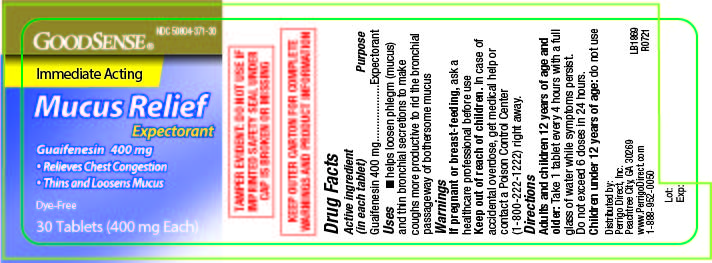 DRUG LABEL: Mucus Relief
NDC: 50804-371 | Form: TABLET
Manufacturer: Good Sense
Category: otc | Type: HUMAN OTC DRUG LABEL
Date: 20210505

ACTIVE INGREDIENTS: GUAIFENESIN 400 mg/1 1
INACTIVE INGREDIENTS: CROSCARMELLOSE SODIUM; MICROCRYSTALLINE CELLULOSE; SILICON DIOXIDE; STEARIC ACID; DIBASIC CALCIUM PHOSPHATE DIHYDRATE; POVIDONE

370 - Mucus Relief

Active ingredient(s)

Guaifenesin 400 mg

Purpose

Expectorant

Use(s)

helps loosen phlegm (mucus)and thin bronchial secretions to make
coughs more productive to rid the bronchial passageway of bothersome mucus

Warnings

Ask a doctor before use if

you have

- persistent or chronic cough such as occurs with smoking, asthma, chronic bronchitis or emphysema
- cough accompanied by excessive phlegm (mucus)

When using this product

- do not exceed recommended dosage

- do not use for more than 7 days

Stop use and ask a doctor if

- cough lasts for more than 7 days, recurs, or is accompanied by fever, rash, or persistent headache.

These could be signs of a serious condition.

Pregnancy/Breastfeeding

ask a healthcare professional before use.

Keep out of reach of children

In case of accidental overdose, get medical help or contact a Poison Control Center (1-800-222-1222) right away.

Directions

Adults and children12 years of age and older: Take 1 tablet every 4 hours with a full glass of water while symptoms persist. Do not exceed 6 doses in 24 hours.

Children under12 years of age: do not use

Other information

- do not use if imprinted safety seal under cap is broken or missing

Storage

- store at 25°C (77°F) excursions between 15° to 30°C (59° to 86°F)

- keep in a dry place and do not expose to heat

Inactive ingredients

Croscarmellose Sodium, Maltodextrin, Microcrystalline Cellulose, Povidone, Silicon Dioxide, Stearic Acid

Questions

Call 1-800-719-9260 Monday through Friday 9AM – 5PM EST.

Principal Display Panel

Mucus Relief
Mucus Relief